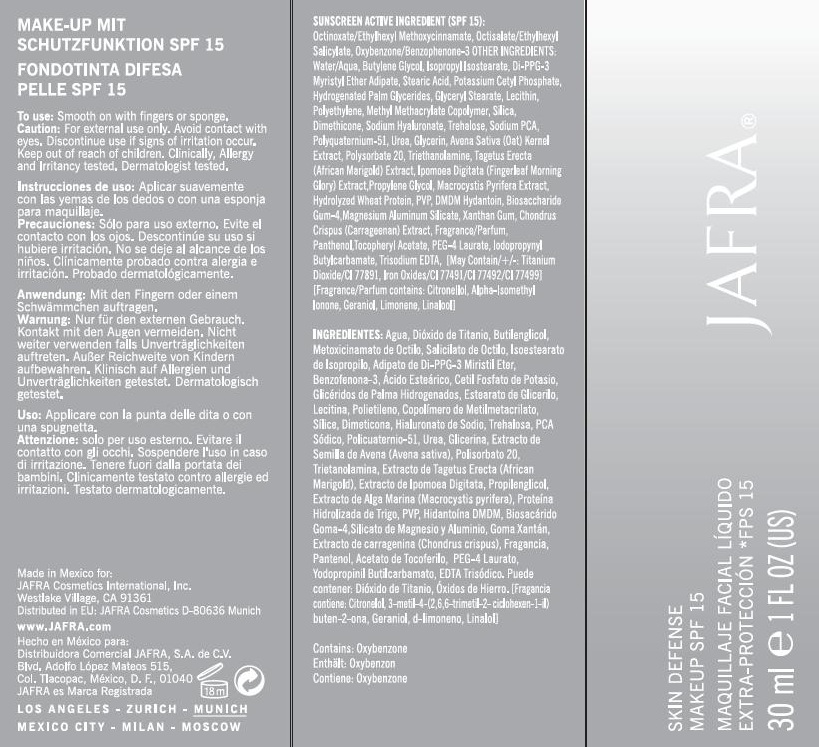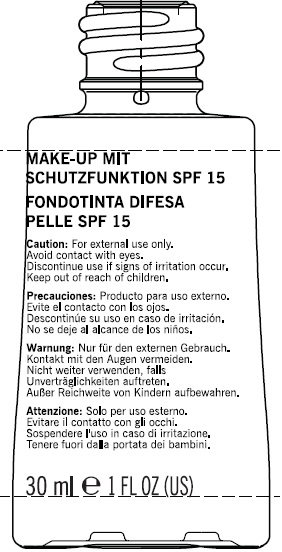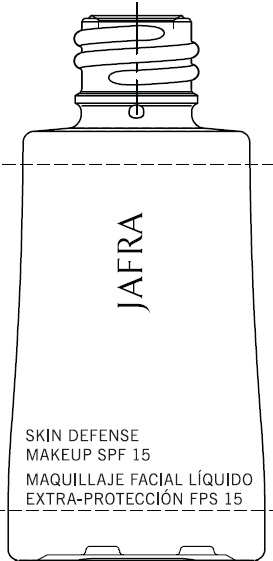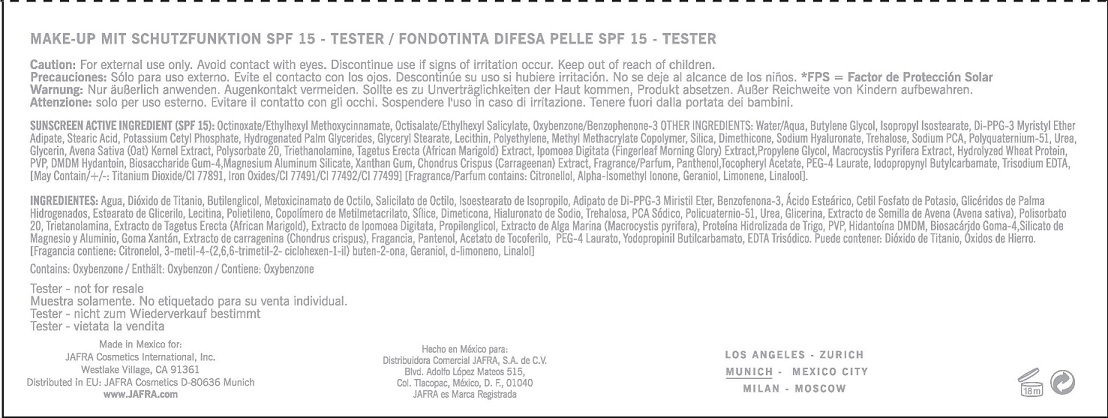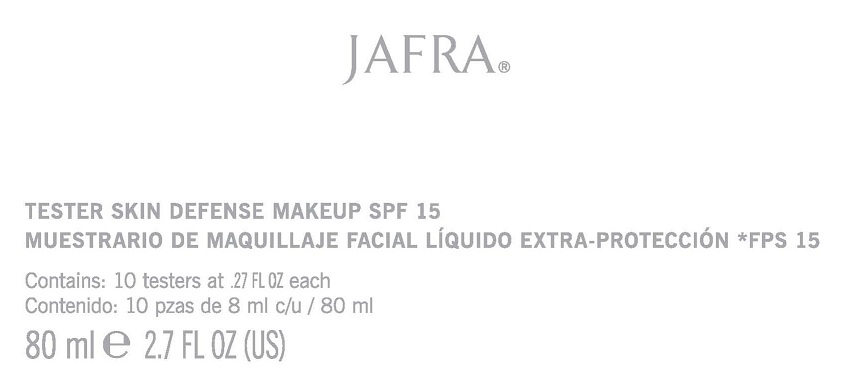 DRUG LABEL: SKIN DEFENSE MAKEUP
NDC: 68828-147 | Form: LOTION
Manufacturer: JAFRA COSMETICS INTERNATIONAL
Category: otc | Type: HUMAN OTC DRUG LABEL
Date: 20120523

ACTIVE INGREDIENTS: OCTINOXATE 6 g/100 mL; OCTISALATE 3 g/100 mL; OXYBENZONE 2 g/100 mL
INACTIVE INGREDIENTS: WATER; BUTYLENE GLYCOL; ISOPROPYL ISOSTEARATE; DI-PPG-3 MYRISTYL ETHER ADIPATE; STEARIC ACID; POTASSIUM CETYL PHOSPHATE; HYDROGENATED PALM GLYCERIDES; GLYCERYL MONOSTEARATE; LECITHIN, SOYBEAN; ZINC OXIDE; HIGH DENSITY POLYETHYLENE; METHYL METHACRYLATE; SILICON DIOXIDE; DIMETHICONE; HYALURONATE SODIUM; TREHALOSE; SODIUM PYRROLIDONE CARBOXYLATE; POLIDRONIUM CHLORIDE; UREA; GLYCERIN; OAT; POLYSORBATE 20; TROLAMINE; TAGETES ERECTA FLOWER; IPOMOEA MAURITIANA TUBER; PROPYLENE GLYCOL; MACROCYSTIS PYRIFERA; HYDROLYZED WHEAT PROTEIN (ENZYMATIC, 3000 MW); POVIDONE K30; DMDM HYDANTOIN; BIOSACCHARIDE GUM-1; MAGNESIUM ALUMINUM SILICATE; XANTHAN GUM; CHONDRUS CRISPUS; PANTHENOL; ALPHA-TOCOPHEROL ACETATE; PEG-4 LAURATE; IODOPROPYNYL BUTYLCARBAMATE; EDETATE TRISODIUM; TITANIUM DIOXIDE; FERRIC OXIDE RED; FERRIC OXIDE YELLOW; FERROSOFERRIC OXIDE

SKIN DEFENSE MAKEUP SPF-15

SUNSCREEN ACTIVE INGREDIENT (SPF 15):
OCTINOXATE/ETHYLHEXYL METHOXYCINNAMATE, OCTISALATE/ETHYLHEXYL SALICYLATE, OXYBENZONE/BENZOPHENONE-3

PURPOSE: SUNSCREEN

INACTIVE INGREDIENT

OTHER INGREDIENTS: WATER/AQUA, BUTYLENE GLYCOL, ISOPROPYL ISOSTEARATE, DI-PPG-3 MYRISTYL ETHER ADIPATE, STEARIC ACID, POTASSIUM CETHYL PHOSPHATE, HYDROGENATED PALM GLYCERIDES, GLYCERYL STEARATE, LECITHIN, POLYETHYLENE, METHYL METHACRYLATE COPOLYMER, SILICA, DIMETHICONE, SODIUM HYALURONATE, TREHALOSE, SODIUM PCA, POLYQUATERNIUM-51, UREA, GLYCERIN, AVENA SATIVA (OAT) KERNEL EXTRACT, POLYSORBATE 20, TRIETHANOLAMINE, TAGETUS ERECTA (AFRICAN MARIGOLD) EXTRACT, IPOMOEA DIGITATA (FINGERLEAF MORNING GLORY) EXTRACT, PROPYLENE GLYCOL, MACROCYSTIS PYRIFERA EXTRACT, HYDROLYZED WHEAT PROTEIN, PVP, DMDM HYDANTOIN, BIOSACCHARIDE GUM-4, MAGNESIUM ALUMINUM SILICATE, XANTHAN GUM, CHONDRUS CRISPUS (CARRAGEENAN) EXTRACT, FRAGRANCE/PARFUM, PANTHENOL, TOCOPHERYL ACETATE, PEG-4 LAURATE, IODOPROPYNYL BUTYLCARBAMATE, TRISODIUM EDTA [MAY CONTAIN, +/-: TITANIUM DIOXIDE/CI 77891, IRON OXIDES/CI 77491/CI 77492/CI 77499] [FRAGRANCE/PARFUM CONTAINS: CITRONELLOL, ALPHA-ISOMETHYL IONONE, GERANIOL, LIMONENE, LINALOOL].

INDICATIONS AND USAGE

SPF 15 PROTECTS AGAINST DAMAGING ULTRAVIOLET RAYS. MATTE FINISH. SHEER TO MEDIUM COVERAGE.

TO USE: SMOOTH ON WITH FINGERS OR SPONGE.

WARNINGS

CAUTION: FOR EXTERNAL USE ONLY. AVOID CONTACT WITH EYES.

DISCONTINUE USE IF SIGNS OF IRRITATION OCCUR.

KEEP OUT OF REACH OF CHILDREN.

PACKAGE LABEL

JAFRA

SKIN DEFENSE MAKEUP SPF 15